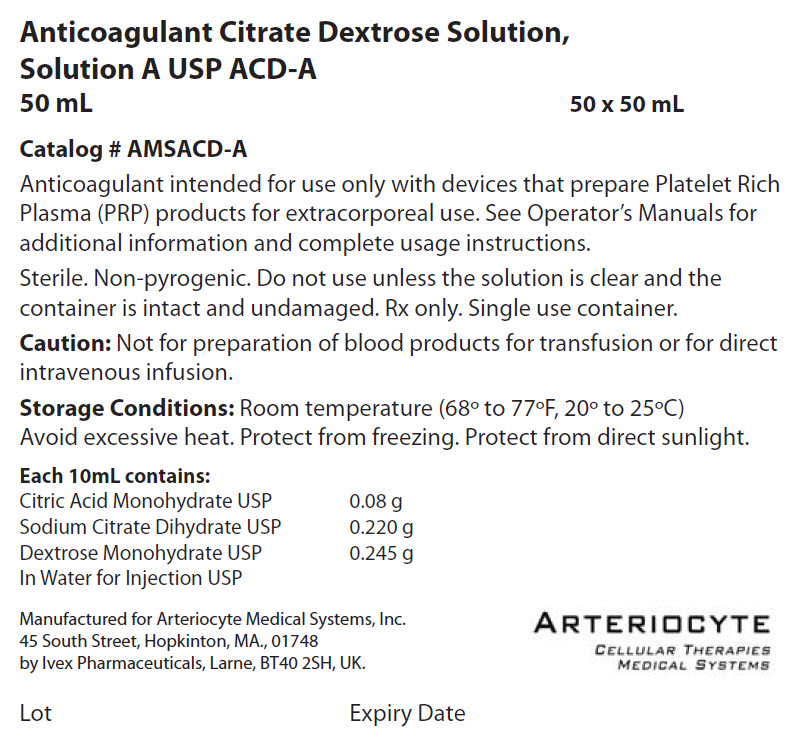 DRUG LABEL: Anticoagulant Citrate Dextrose A ACD-A
NDC: 43203-852 | Form: INJECTION, SOLUTION
Manufacturer: Arteriocyte Medical Systems, Inc.
Category: prescription | Type: HUMAN PRESCRIPTION DRUG LABEL
Date: 20250123

ACTIVE INGREDIENTS: CITRIC ACID MONOHYDRATE 0.08 g/10 mL; SODIUM CITRATE, UNSPECIFIED FORM 0.220 g/10 mL; DEXTROSE MONOHYDRATE 0.245 g/10 mL
INACTIVE INGREDIENTS: Water 9.76 g/10 mL

Anticoagulant Citrate Dextrose Solution,
Solution A, USP

ACD-A 50 mL
Catalog # AMSACD-A

Anticoagulant intended for use only with devices that prepare Platelet Rich Plasma (PRP) products for extracorporeal use. See Operator's Manuals for additional information and complete usage instructions.

Sterile. Non-pyrogenic. Do not use unless the solution is clear and the container is intact and undamaged.

Rx only. Single use container.

Caution

Not for preparation of blood products for transfusion or for direct intravenous infusion.

Recommended storage

Room temperature (68° to 77°F, 20° to 25°C)

Avoid excessive heat. Protect from freezing.

Each 10mL contains

Citric Acid Monohydrate USP | 0.08 g
Sodium Citrate Dihydrate USP | 0.220 g
Dextrose Monohydrate USP | 0.245 g
In Water for Injection USP

Manufactured for Arteriocyte Medical Systems, Inc.
45 South Street, Hopkinton, MA., 01748
by Ivex Pharmaceuticals, Larne, BT40 2SH, UK.

ARTERIOCYTE
CELLULAR THERAPIES
MEDICAL SYSTEMS

Lot
Expiry Date

PRINCIPAL DISPLAY PANEL - 50 Pouch Case Label

Anticoagulant Citrate Dextrose Solution,
Solution A USP ACD-A

50 mL
50 x 50 mL

Catalog # AMSACD-A

Anticoagulant intended for use only with devices that prepare Platelet Rich
Plasma (PRP) products for extracorporeal use. See Operator's Manuals for
additional information and complete usage instructions.

Sterile. Non-pyrogenic. Do not use unless the solution is clear and the
container is intact and undamaged. Rx only. Single use container.

Caution: Not for preparation of blood products for transfusion or for direct
intravenous infusion.

Storage Conditions: Room temperature (68° to 77°F, 20° to 25°C)
Avoid excessive heat. Protect from freezing. Protect from direct sunlight.

Each 10mL contains:

Citric Acid Monohydrate USP
0.08 g
Sodium Citrate Dihydrate USP
0.220 g
Dextrose Monohydrate USP
0.245 g
In Water for Injection USP

Manufactured for Arteriocyte Medical Systems, Inc.
45 South Street, Hopkinton, MA., 01748
by Ivex Pharmaceuticals, Larne, BT40 2SH, UK.

ARTERIOCYTE
CELLULAR THERAPIES
MEDICAL SYSTEMS

Lot
Expiry Date